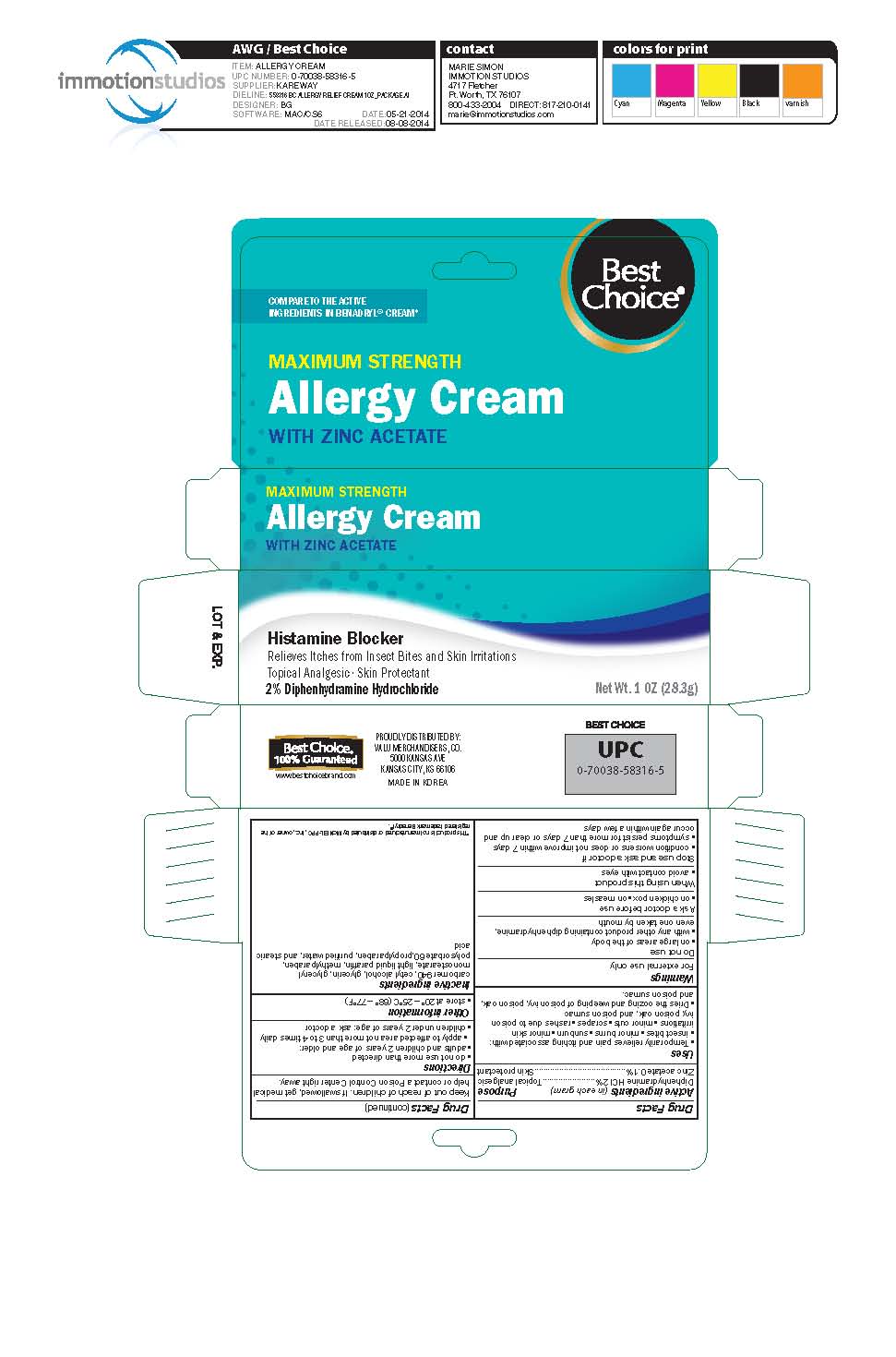 DRUG LABEL: Allergic Itch Relief
NDC: 63941-316 | Form: CREAM
Manufacturer: Valu Merchandisers, Co.
Category: otc | Type: HUMAN OTC DRUG LABEL
Date: 20230208

ACTIVE INGREDIENTS: DIPHENHYDRAMINE HYDROCHLORIDE 2 g/100 g; ZINC ACETATE 0.1 g/100 g
INACTIVE INGREDIENTS: CARBOMER HOMOPOLYMER TYPE C; CETYL ALCOHOL; GLYCERIN; GLYCERYL MONOSTEARATE; PARAFFIN; METHYLPARABEN; POLYSORBATE 60; STEARIC ACID; PROPYLPARABEN; WATER

Best Choice Allergy Cream

Active ingredients (in each gram)

Diphenhydramine HCl 2%

Zinc acetate 0.1%

Purpose

Topical analgesic

Skin protectant

Uses

- temporarily relieves itching and pain associated with
- insect bites
- minor burns
- sunburn
- minor skin irritations
- minor cuts
- scrapes
- rashes due to poison ivy, poison oak or poison sumac
- dries the oozing and weeping of poison ivy, poison oak, and poison sumac

Warnings

For external use only

Do not use

- on large areas of the body
- with any other product containing diphenhydramine, even one taken by mouth

Ask a doctor before use

- on chicken pox
- on measles

When using this product

- avoid contact with eyes

Stop use and ask a doctor if

- condition worsens or does not improve within 7 days
- symptoms persist for more than 7 days or clear up and occur again within a few days

Keep out of reach of children.

If swallowed, get medical help or contact a Poison Control Center right away.

Directions

- do not use more often than directed
- adults and children 12 years of age and over: apply to affected area not more than 3 to 4 times daily
- children under 12 years of age: ask a doctor

Other information

- store at 59° to 77°F

Inactive ingredients

carbomer 940, cetyl alcohol, glycerin, glyceryl monostearate, light liquid paraffin, methylparaben, polysorbate 60, propylparaben, purified water, and stearic acid

Package label

Anti-Itch Cream